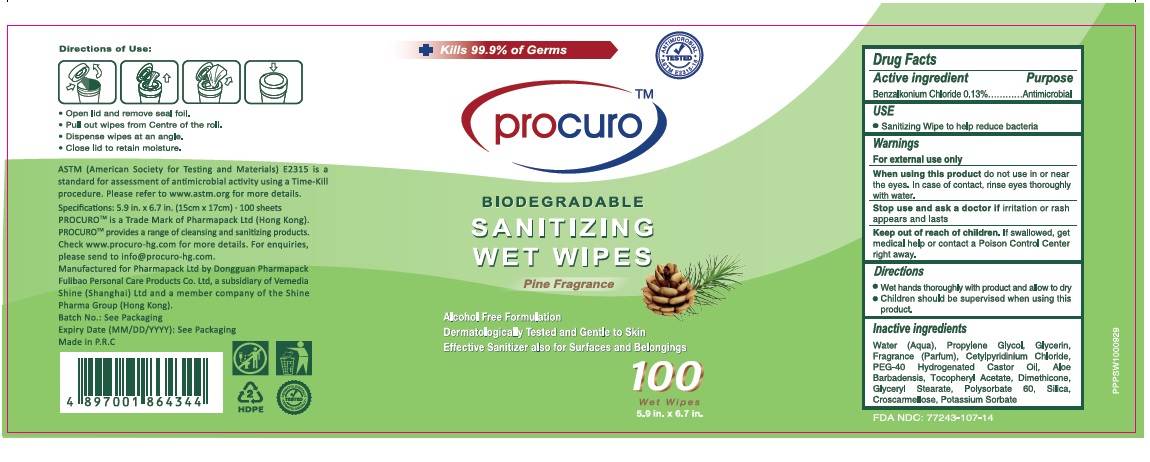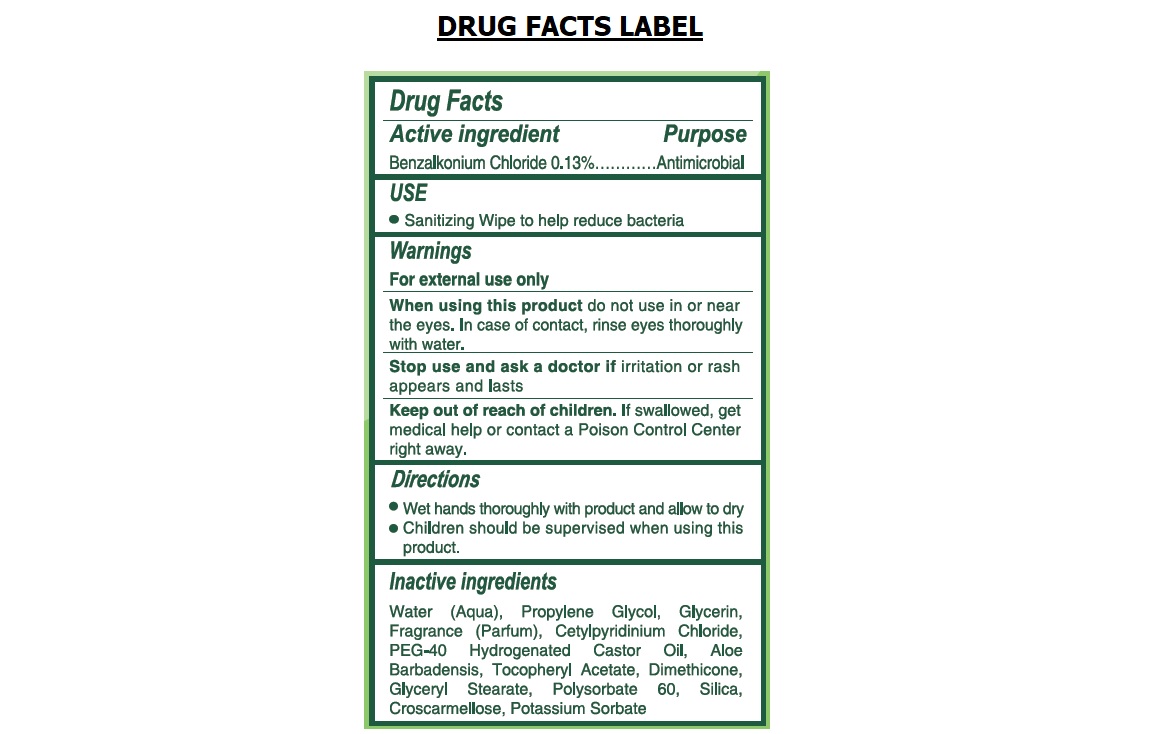 DRUG LABEL: Procuro SANITIZING WET WIPES - Pine Fragrance
NDC: 77243-107 | Form: CLOTH
Manufacturer: Dongguan Pharmapack Fulibao Personal Care Products Ltd
Category: otc | Type: HUMAN OTC DRUG LABEL
Date: 20240130

ACTIVE INGREDIENTS: BENZALKONIUM CHLORIDE 0.13 g/100 mL
INACTIVE INGREDIENTS: WATER; PROPYLENE GLYCOL; GLYCERIN; CETYLPYRIDINIUM CHLORIDE; POLYOXYL 40 HYDROGENATED CASTOR OIL; ALOE VERA LEAF; .ALPHA.-TOCOPHEROL ACETATE; DIMETHICONE; GLYCERYL MONOSTEARATE; POLYSORBATE 60; SILICON DIOXIDE; CROSCARMELLOSE; POTASSIUM SORBATE

procuroTMSANITIZING WET WIPES

Active ingredient

Benzalkonium Chloride 0.13%

Purpose

Antimicrobial

USE

• Sanitizing Wipe to help reduce bacteria

Warnings

For external use only

When using this productdo not use in or near the eyes. In case of contact, rinse eyes thoroughly with water.

Stop use and ask a doctor ifirritation or rash appears and lasts

Keep out of reach of children.If swallowed, get medical help or contact a Poison Control Center right away.

Directions

• Wet hands thoroughly with product and allow to dry

• Children should be supervised when using this product.

Inactive ingredients

Water (Aqua), Propylene Glycol, Glycerin, Fragrance (Parfum), Cetylpyridinium Chloride, PEG-40 Hydrogenated Castor Oil, Aloe Barbadensis, Tocopheryl Acetate, Dimethicone, Glyceryl Stearate, Polysorbate 60, Silica, Croscarmellose, Potassium Sorbate

Kills 99.9% of Germs

BIODEGRADABLE

Pine Fragrance

Alcohol Free Formulation

Dermatologically Tested and Gentle to skin

Effective Sanitizer also for Surfaces and belongings

ANTIMICROBIAL • ASTM E2315-16 • TESTED

Directions of Use:

•Open lid and remove seal foil.

•Pull out wipes from Centre of the roll.

•Dispense wipes at an angle.

•Close lid to retain moisture.

ASTM (American Society for Testing and Materials) E2315 is a standard for assessment of antimicrobial activity using a Time-Kill procedure. Please refer to www.astm.org for more details.

PROCUROTM is a Trade Mark of Pharmapack Ltd (Hong Kong). PROCUROTM provides a range of cleansing and sanitizing products.

Check www. procuro-hg.com for more details. For enquiries, please send to info@ procuro-hg.com

Manufactured for Pharmapack Ltd by Dongguan Pharmapack Fulibao Personal Care Products Co. Ltd, a subsidiary of Vemedia Shine (Shanghai) Ltd and a member company of the Shine Pharma Group (Hong Kong).

Made in P.R.C